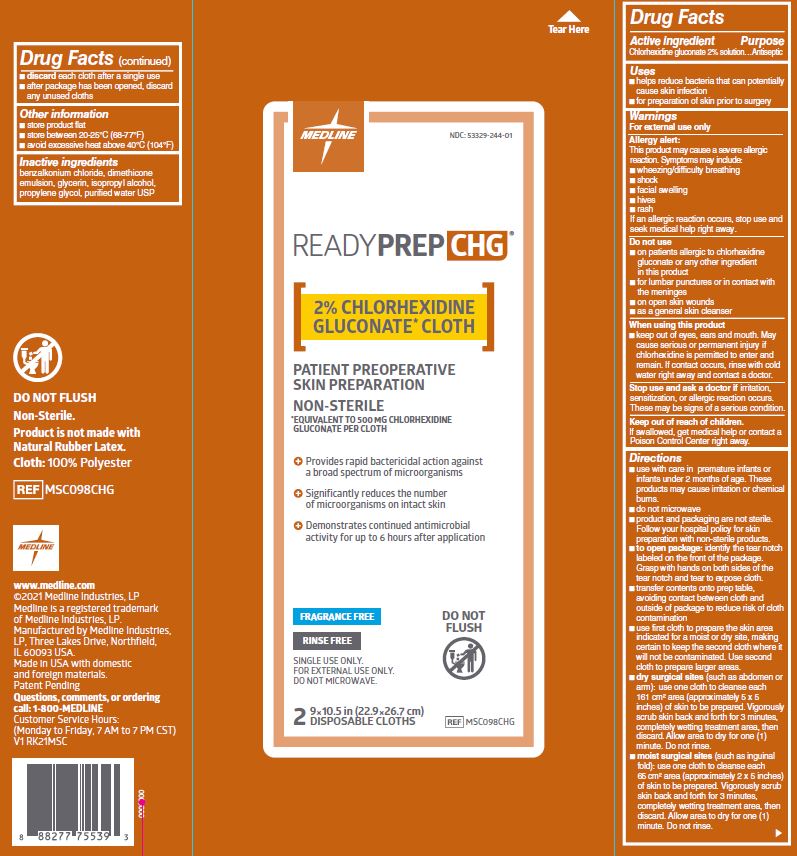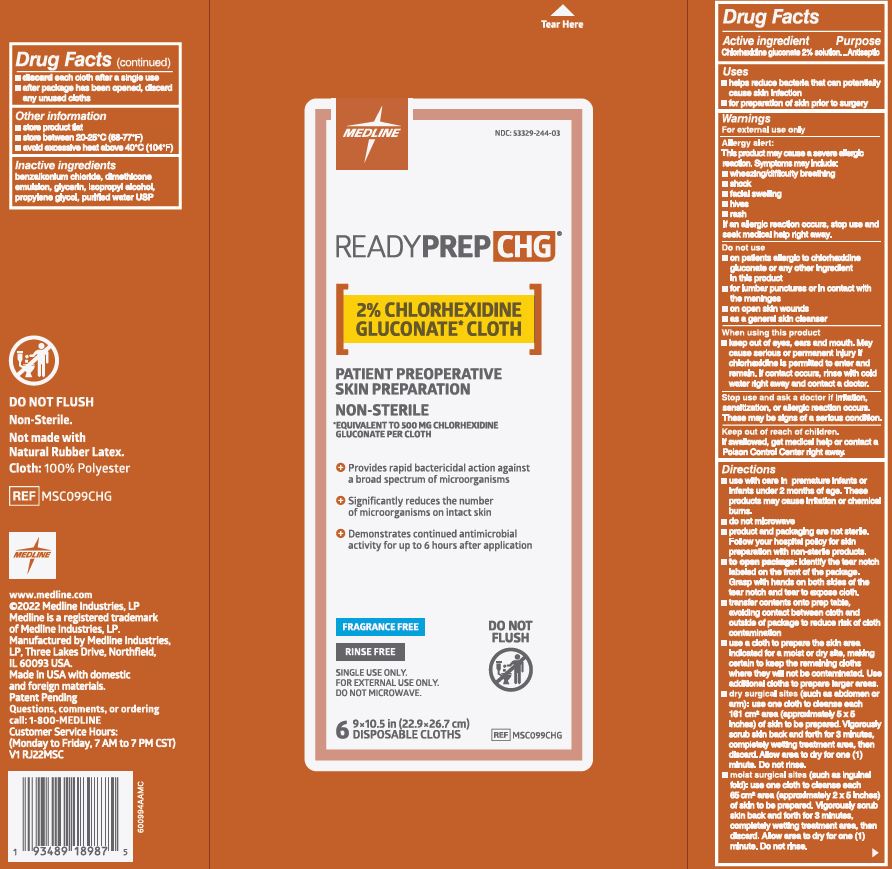 DRUG LABEL: ReadyPrep CHG
NDC: 53329-244 | Form: CLOTH
Manufacturer: Medline Industries, LP
Category: otc | Type: HUMAN OTC DRUG LABEL
Date: 20240909

ACTIVE INGREDIENTS: CHLORHEXIDINE GLUCONATE 500 mg/1 1
INACTIVE INGREDIENTS: GLYCERIN; WATER; DIMETHICONE 350; PROPYLENE GLYCOL; BENZALKONIUM CHLORIDE; ISOPROPYL ALCOHOL

244 ReadyPrep CHG

Active ingredient

Chlorhexidine gluconate 2% solution

Purpose

Antiseptic

Uses

- helps reduce bacteria that can potentially cause skin infection
- for preparation of skin prior to surgery

Warnings

For external use only

Allergy alert:

This product may cause a severe allergic reaction. Symptoms may include:

- wheezing/difficulty breathing
- shock
- facial swelling
- hives
- rash

If an allergic reaction occurs, stop use and seek medical help right away.

Do not use

- on patients allergic to chlorhexidine gluconate or any other ingredient in this product
- for lumbar punctures or in contact with the meninges
- on open skin wounds
- as a general skin cleanser

Stop use and ask a doctor if

irritation, sensitization, or allergic reaction occurs. These may be signs of a serious condition.

When using this product

- keep out of eyes, ears and mouth. May cause serious or permanent injury if chlorhexidine is permitted to enter and remain. If contact occurs, rinse with cold water right away and contact a doctor.

Keep out of reach of children.

If swallowed, get medical help or contact a Posion Control Center right away.

Directions

- use with care in premature infants or infants under 2 months of age. These products may cause irritation or chemical burns.
- do not microwave
- product and packaging are not sterile. Follow your hospital policy for skin preparation with non-sterile products.
- to open package: identify the tear notch labeled on the front of the package. Grasp with both hands on both sides of the tear notch and tear to expose cloth.
- transfer contents onto prep table, avoiding contact between cloth and outside of package to reduce risk of cloth contamination
- use [first/a] cloth to prepare the skin area indicated for a moist or dry site, making certain to keep the [second/remaining] cloth[s] where it will not be contaminated. Use [second/additional] cloth to prepare larger areas.
- dry surgical sites: (such as abdomen or arm): use one cloth to cleanse each 161 cm^2 area (approximately) 5 x 5 inches) of skin to be prepared. Vigorously scrub skin back and forth for 3 minutes, completely wetting treatment area, then discard. Allow area to dry for one (1) minute. Do not rinse.
- moist surgical sites (such as inguinal fold): use one cloth to cleanse each 65 cm^2 area (approximately 2 x 5 inches) of skin to be prepared. Vigorously scrub skin back and forth for 3 minutes, competely wetting treatment area, then discard. Allow area to dry for one (1) minute. Do not rinse.
- discard each cloth after a single use
- after package has been opened, discard any unused cloths

Other information

- store product flat
- store between 20-25°C (68-77°F)
- avoid excessive heat above 40°C (104°F)

Inactive ingredients

- benzalkonium chloride
- dimethicone emulsion
- glycerin
- isopropyl alcohol
- propylene glycol
- purified water USP

Manufacturing Information

DO NOT FLUSH

Non-Sterile.

Product is not made with Natural Rubber Latex.

Cloth: 100% Polyester

REF MSC098CHG, MSC099CHG

www.medline.com

©2021 Medline Industries, LP

Medline is a registered trademark of Medline Industries, LP

Manufactured by

Medline Industries, LP

Northfield, IL 60093 USA.

Made in USA with domestic and foreign materials.

Patent Pending

Questions, comments, or ordering call: 1-800-MEDLINE (633-5463)

Customer Service Hours:

(Monday to Friday, 7 AM to 7 PM CST)

V1 RK21MSC, V1 RJ22MSC

Recent Major Changes

December 2022: Additional verbiage added to " Directions" section due to the 6 count product (NDC: 53329-244-03) being added to the SPL per S-003 (supplement 3).